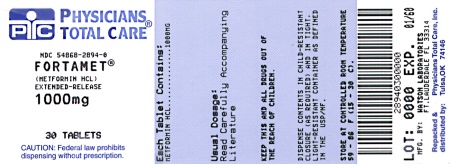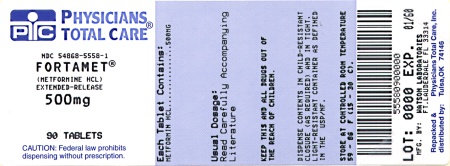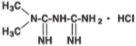 DRUG LABEL: Fortamet
NDC: 54868-5558 | Form: TABLET, EXTENDED RELEASE
Manufacturer: Physicians Total Care, Inc.
Category: prescription | Type: HUMAN PRESCRIPTION DRUG LABEL
Date: 20100315

ACTIVE INGREDIENTS: METFORMIN HYDROCHLORIDE 500 mg/1 1
INACTIVE INGREDIENTS: CANDELILLA WAX; CELLULOSE ACETATE; HYPROMELLOSE; MAGNESIUM STEARATE; POLYETHYLENE GLYCOL; POLYSORBATE 80; POVIDONE; SODIUM LAURYL SULFATE; FERROSOFERRIC OXIDE; TITANIUM DIOXIDE; TRIACETIN

WARNINGS

Lactic Acidosis:

Lactic acidosis is a rare, but serious, metabolic complication that can occur due to metformin accumulation during treatment with FORTAMET® (metformin hydrochloride) Extended-Release Tablets; when it occurs, it is fatal in approximately 50% of cases. Lactic acidosis may also occur in association with a number of pathophysiologic conditions, including diabetes mellitus, and whenever there is significant tissue hypoperfusion and hypoxemia. Lactic acidosis is characterized by elevated blood lactate levels (>5 mmol/ L), decreased blood pH, electrolyte disturbances with an increased anion gap, and an increased lactate/pyruvate ratio. When metformin is implicated as the cause of lactic acidosis, metformin plasma levels >5 μg/mL are generally found.

The reported incidence of lactic acidosis in patients receiving metformin hydrochloride is very low (approximately 0.03 cases/1000 patient-years, with approximately 0.015 fatal cases/1000 patient-years). Reported cases have occurred primarily in diabetic patients with significant renal insufficiency, including both intrinsic renal disease and renal hypoperfusion, often in the setting of multiple concomitant medical/ surgical problems and multiple concomitant medications. Patients with congestive heart failure requiring pharmacologic management, in particular those with unstable or acute congestive heart failure who are at risk of hypoperfusion and hypoxemia, are at increased risk of lactic acidosis. The risk of lactic acidosis increases with the degree of renal dysfunction and the patient's age. The risk of lactic acidosis may, therefore, be significantly decreased by regular monitoring of renal function in patients taking FORTAMET® (metformin hydrochloride) Extended-Release Tablets and by use of the minimum effective dose of FORTAMET®. In particular, treatment of the elderly should be accompanied by careful monitoring of renal function. FORTAMET® treatment should not be initiated in patients ≥80 years of age unless measurement of creatinine clearance demonstrates that renal function is not reduced, as these patients are more susceptible to developing lactic acidosis. In addition, FORTAMET® should be promptly withheld in the presence of any condition associated with hypoxemia, dehydration, or sepsis. Because impaired hepatic function may significantly limit the ability to clear lactate, FORTAMET® should generally be avoided in patients with clinical or laboratory evidence of hepatic disease. Patients should be cautioned against excessive alcohol intake, either acute or chronic, when taking FORTAMET®, since alcohol potentiates the effects of metformin hydrochloride on lactate metabolism. In addition, FORTAMET® should be temporarily discontinued prior to any intravascular radiocontrast study and for any surgical procedure (see also PRECAUTIONS).

The onset of lactic acidosis often is subtle, and accompanied only by nonspecific symptoms such as malaise, myalgias, respiratory distress, increasing somnolence, and nonspecific abdominal distress. There may be associated hypothermia, hypotension, and resistant bradyarrhythmias with more marked acidosis. The patient and the patient's physician must be aware of the possible importance of such symptoms and the patient should be instructed to notify the physician immediately if they occur (see also PRECAUTIONS). FORTAMET® should be withdrawn until the situation is clarified. Serum electrolytes, ketones, blood glucose and, if indicated, blood pH, lactate levels, and even blood metformin levels may be useful. Once a patient is stabilized on any dose level of FORTAMET®, gastrointestinal symptoms, which are common during initiation of therapy, are unlikely to be drug related. Later occurrence of gastrointestinal symptoms could be due to lactic acidosis or other serious disease.

Levels of fasting venous plasma lactate above the upper limit of normal but less than 5 mmol/L in patients taking FORTAMET® do not necessarily indicate impending lactic acidosis and may be explainable by other mechanisms, such as poorly controlled diabetes or obesity, vigorous physical activity, or technical problems in sample handling (see also PRECAUTIONS).

Lactic acidosis should be suspected in any diabetic patient with metabolic acidosis lacking evidence of ketoacidosis (ketonuria and ketonemia).

Lactic acidosis is a medical emergency that must be treated in a hospital setting. In a patient with lactic acidosis who is taking FORTAMET®, the drug should be discontinued immediately and general supportive measures promptly instituted. Because metformin hydrochloride is dialyzable (with a clearance of up to 170 mL/min under good hemodynamic conditions), prompt hemodialysis is recommended to correct the acidosis and remove the accumulated metformin. Such management often results in prompt reversal of symptoms and recovery (see also CONTRAINDICATIONS and PRECAUTIONS).

DESCRIPTION

FORTAMET® (metformin hydrochloride) Extended-Release Tablets contain an oral antihyperglycemic drug used in the management of type 2 diabetes. Metformin hydrochloride (N, N-dimethylimidodicarbonimidic diamide hydrochloride) is a member of the biguanide class of oral antihyperglycemics and is not chemically or pharmacologically related to any other class of oral antihyperglycemic agents. The empirical formula of metformin hydrochloride is C4H11N5•HCl and its molecular weight is 165.63. Its structural formula is:

Metformin hydrochloride is a white to off-white crystalline powder that is freely soluble in water and is practically insoluble in acetone, ether, and chloroform. The pKa of metformin is 12.4. The pH of a 1% aqueous solution of metformin hydrochloride is 6.68.

FORTAMET® Extended-Release Tablets are designed for once-a-day oral administration and deliver 500 mg or 1000 mg of metformin hydrochloride. In addition to the active ingredient metformin hydrochloride, each tablet contains the following inactive ingredients: candellila wax, cellulose acetate, hypromellose, magnesium stearate, polyethylene glycols (PEG 400, PEG 8000), polysorbate 80, povidone, sodium lauryl sulfate, synthetic black iron oxides, titanium dioxide, and triacetin.

FORTAMET® meets USP Dissolution Test 5.

SYSTEM COMPONENTS AND PERFORMANCE

FORTAMET® was developed as an extended-release formulation of metformin hydrochloride and designed for once-a-day oral administration using the patented single-composition osmotic technology (SCOT™). The tablet is similar in appearance to other film-coated oral administered tablets but it consists of an osmotically active core formulation that is surrounded by a semipermeable membrane. Two laser drilled exit ports exist in the membrane, one on either side of the tablet. The core formulation is composed primarily of drug with small concentrations of excipients. The semipermeable membrane is permeable to water but not to higher molecular weight components of biological fluids. Upon ingestion, water is taken up through the membrane, which in turn dissolves the drug and excipients in the core formulation. The dissolved drug and excipients exit through the laser drilled ports in the membrane. The rate of drug delivery is constant and dependent upon the maintenance of a constant osmotic gradient across the membrane. This situation exists so long as there is undissolved drug present in the core tablet. Following the dissolution of the core materials, the rate of drug delivery slowly decreases until the osmotic gradient across the membrane falls to zero at which time delivery ceases. The membrane coating remains intact during the transit of the dosage form through the gastrointestinal tract and is excreted in the feces.

CLINICAL PHARMACOLOGY

Mechanism of Action

Metformin is an antihyperglycemic agent which improves glucose tolerance in patients with type 2 diabetes, lowering both basal and postprandial plasma glucose. Its pharmacologic mechanisms of action are different from other classes of oral antihyperglycemic agents. Metformin decreases hepatic glucose production, decreases intestinal absorption of glucose, and improves insulin sensitivity by increasing peripheral glucose uptake and utilization. Unlike sulfonylureas, metformin does not produce hypoglycemia in either patients with type 2 diabetes or normal subjects (except in special circumstances, see PRECAUTIONS) and does not cause hyperinsulinemia. With metformin therapy, insulin secretion remains unchanged while fasting plasma insulin levels and day-long plasma insulin response may actually decrease.

PHARMACOKINETICS AND DRUG METABOLISM

Enter section text here

Absorption and Bioavailability

The appearance of metformin in plasma from a FORTAMET® Extended-Release Tablet is slower and more prolonged compared to immediate-release metformin.

In a multiple-dose crossover study, 23 patients with type 2 diabetes mellitus were administered either FORTAMET® 2000 mg once a day (after dinner) or immediate-release (IR) metformin hydrochloride 1000 mg twice a day (after breakfast and after dinner). After 4 weeks of treatment, steady-state pharmacokinetic parameters, area under the concentration-time curve (AUC), time to peak plasma concentration (Tmax), and maximum concentration (Cmax) were evaluated. Results are presented in Table 1.

Table 1 FORTAMET® vs. Immediate-Release Metformin Steady-State Pharmacokinetic Parameters at 4 Weeks
Pharmacokinetic Parameters (mean ±SD) | FORTAMET® 2000 mg (administered q.d.after dinner) | Immediate-Release Metformin 2000 mg (1000 mg b.i.d.)
AUC 0-24hr (ng•hr/mL) | 26,811 ± 7055 | 27,371 ± 5,781
Tmax (hr) | 6 (3-10) | 3 (1-8)
Cmax (ng/mL) | 2849 ± 797 | 1820 ± 370

In four single-dose studies and one multiple-dose study, the bioavailability of FORTAMET® 2000 mg given once daily, in the evening, under fed conditions [as measured by the area under the plasma concentration versus time curve (AUC)] was similar to the same total daily dose administered as immediate-release metformin 1000 mg given twice daily. The geometric mean ratios (FORTAMET®/ immediate-release metformin) of AUC0-24hr, AUC0-72hr, and AUC0-inf. for these five studies ranged from 0.96 to 1.08.

In a single-dose, four-period replicate crossover design study, comparing two 500 mg FORTAMET® tablets to one 1000 mg FORTAMET® tablet administered in the evening with food to 29 healthy male subjects, two 500 mg FORTAMET® tablets were found to be equivalent to one 1000 mg FORTAMET® tablet.

In a study carried out with FORTAMET®, there was a dose-associated increase in metformin exposure over 24 hours following oral administration of 1000, 1500, 2000, and 2500 mg.

In three studies with FORTAMET® using different treatment regimens (2000 mg after dinner; 1000 mg after breakfast and after dinner; and 2500 mg after dinner), the pharmacokinetics of metformin as measured by AUC appeared linear following multiple-dose administration.

The extent of metformin absorption (as measured by AUC) from FORTAMET® increased by approximately 60% when given with food. When FORTAMET® was administered with food, Cmax was increased by approximately 30% and Tmax was more prolonged compared with the fasting state (6.1 versus 4.0 hours).

Distribution

Distribution studies with FORTAMET® have not been conducted. However, the apparent volume of distribution (V/F) of metformin following single oral doses of immediate-release metformin 850 mg averaged 654 ± 358 L. Metformin is negligibly bound to plasma proteins, in contrast to sulfonylureas, which are more than 90% protein bound. Metformin partitions into erythrocytes, most likely as a function of time. At usual clinical doses and dosing schedules of immediate-release metformin, steady state plasma concentrations of metformin are reached within 24-48 hours and are generally less than 1 μg/mL. During controlled clinical trials of immediate-release metformin, maximum metformin plasma levels did not exceed 5 μg/mL, even at maximum doses.

Metabolism and Excretion

Metabolism studies with FORTAMET® have not been conducted. Intravenous single-dose studies in normal subjects demonstrate that metformin is excreted unchanged in the urine and does not undergo hepatic metabolism (no metabolites have been identified in humans) nor biliary excretion.

In healthy nondiabetic adults (N=18) receiving 2500 mg q.d. FORTAMET®, the percent of the metformin dose excreted in urine over 24 hours was 40.9% and the renal clearance was 542 ± 310 mL/min. After repeated administration of FORTAMET®, there is little or no accumulation of metformin in plasma, with most of the drug being eliminated via renal excretion over a 24-hour dosing interval. The t1/2 was 5.4 hours for FORTAMET®.

Renal clearance of metformin (Table 2) is approximately 3.5 times greater than creatinine clearance, which indicates that tubular secretion is the major route of metformin elimination. Following oral administration, approximately 90% of the absorbed drug is eliminated via the renal route within the first 24 hours, with a plasma elimination half-life of approximately 6.2 hours. In blood, the elimination half-life is approximately 17.6 hours, suggesting that the erythrocyte mass may be a compartment of distribution.

Special Populations

Enter section text here

Geriatrics

Limited data from controlled pharmacokinetic studies of immediate-release metformin in healthy elderly subjects suggest that total plasma clearance of metformin is decreased, the half-life is prolonged, and Cmax is increased, compared to healthy young subjects. From these data, it appears that the change in metformin pharmacokinetics with aging is primarily accounted for by a change in renal function (Table 2). FORTAMET® treatment should not be initiated in patients ≥80 years of age unless measurement of creatinine clearance demonstrates that renal function is not reduced (see WARNINGS, PRECAUTIONS and DOSAGE AND ADMINISTRATION).

Pediatrics

No pharmacokinetic data from studies of pediatric patients are currently available (see PRECAUTIONS).

Gender

Five studies indicated that with FORTAMET® treatment, the pharmacokinetic results for males and females were comparable.

Table 2 Select Mean (±SD) Metformin Pharmacokinetic Parameters Following Single or Multiple Oral Doses of Immediate-Release Metformin
Subject Groups: Immediate-Release Metformin dosea (number of subjects) | Cmax b (μg/mL) | Tmax c (hrs) | Renal Clearance (mL/min)
Healthy, nondiabetic adults:
500 mg single dose (24) | 1.03 (±0.33) | 2.75 (±0.81) | 600 (±132)
850 mg single dose (74)d | 1.60 (±0.38) | 2.64 (±0.82) | 552 (±139)
850 mg three times daily for 19 dosese (9) | 2.01 (±0.42) | 1.79 (±0.94) | 642 (±173)
Adults with type 2 diabetes:
850 mg single dose (23) | 1.48 (±0.5) | 3.32 (±1.08) | 491 (±138)
850 mg three times daily for 19 dosese (9) | 1.90 (±0.62) | 2.01 (±1.22) | 550 (±160)
Elderlyf, healthy nondiabetic adults:
850 mg single dose (12) | 2.45 (±0.70) | 2.71 (±1.05) | 412 (±98)
Renal-impaired adults:850 mg single dose
Mild (CLcrg 61-90 mL/min) (5) | 1.86 (±0.52) | 3.20 (±0.45) | 384 (±122)
Moderate (CLcr 31-60 mL/min) (4) | 4.12 (±1.83) | 3.75 (±0.50) | 108 (±57)
Severe (CLcr 10-30 mL/min) (6) | 3.93 (±0.92) | 4.01 (±1.10) | 130 (±90)

a All doses given fasting except the first 18 doses of the multiple dose studies
b Peak plasma concentration
c Time to peak plasma concentration
d Combined results (average means) of five studies: mean age 32 years (range 23-59 years)
e Kinetic study done following dose 19, given fasting
f Elderly subjects, mean age 71 years (range 65-81 years)
g CLcr = creatinine clearance normalized to body surface area of 1.73 m^2

Renal Insufficiency

In patients with decreased renal function (based on measured creatinine clearance), the plasma and blood half-life of metformin is prolonged and the renal clearance is decreased in proportion to the decrease in creatinine clearance (Table 2; also see WARNINGS).

Hepatic Insufficiency

No pharmacokinetic studies of metformin have been conducted in patients with hepatic insufficiency.

Race

No studies of metformin pharmacokinetic parameters according to race have been performed. In controlled clinical studies of immediate-release metformin in patients with type 2 diabetes, the antihyperglycemic effect was comparable in whites (n=249), blacks (n=51), and Hispanics (n=24).

Clinical Studies

In a double-blind, randomized, active-controlled, multicenter U.S. clinical study, which compared FORTAMET® q.d. to immediate-release metformin b.i.d., 680 patients with type 2 diabetes who had been taking metformin-containing medication at study entry were randomly assigned in equal numbers to double-blind treatment with either FORTAMET® or immediate-release metformin. Doses were adjusted during the first six weeks of treatment with study medication based on patients' FPG levels and were then held constant over a period of 20 weeks. The primary efficacy endpoint was the change in HbA1c from baseline to endpoint. The primary objective was to demonstrate the clinical non-inferiority of FORTAMET® compared to immediate-release metformin on the primary endpoint.

FORTAMET® and metformin patients had mean HbA1c changes from baseline to endpoint equal to +0.40 and +0.14, respectively (Table 3). The least-square (LS) mean treatment difference was 0.25 (95% CI = 0.14, 0.37) demonstrating that FORTAMET® was clinically similar to metformin according to the pre-defined criterion to establish efficacy.

Table 3 FORTAMET® vs. Immediate-Release Metformin Switch Study: Summary of Mean Changes in HbA1c, Fasting Plasma Glucose, Body Weight, Body Mass Index, and Plasma Insulin
 | FORTAMET® | Immediate-Release Metformin | Treatment difference for change from baseline (FORTAMET® minus Immediate-Release Metformin) LS mean (2 sided 95% CIa)
HbA1c (%)
N | 327 | 332 | 0.25
Baseline (mean ± SD) | 7.04 ± 0.88 | 7.07 ± 0.76 | (0.14,0.37)b
Change from baseline (mean ± SD) | 0.40 ± 0.75 | 0.14 ± 0.75
Fasting Plasma Glucose (mg/dL)
N | 329 | 333 | 6.43
Baseline (mean ± SD) | 146.8 ± 32.1 | 145.6 ± 29.5 | (0.57, 12.29)
Change from baseline (mean ± SD) | 10.0 ± 40.8 | 4.2 ± 35.9
Plasma Insulin (μu/mL)
N | 304 | 316 | 0.02
Baseline (mean ± SD) | 17.9 ± 15.1 | 17.3 ± 10.5 | (-1.47, 1.50)
Change from baseline (mean ± SD) | -3.6 ± 13.8 | -3.2 ± 8.6
Body Weight (kg)
N | 313 | 320 | 0.30
Baseline (mean ± SD) | 94.1 ± 17.8 | 93.3 ± 17.4 | (-0.22, 0.81)
Change from baseline(mean ± SD) | 0.3 ± 2.9 | 0.0 ± 3.7
Body Mass Index (kg/m^2)
N | 313 | 320 | 0.08
Baseline (mean ± SD) | 31.1 ±4.7 | 31.4 ± 4.5 | (-0.11, 0.26)
Change from baseline(mean ± SD) | 0.1 ± 1.1 | 0.0 ± 1.3

a CI=Confidence Interval

b FORTAMET® was clinically similar to immediate-release metformin based on the pre-defined criterion to establish efficacy. While demonstrating clinical similarity, the response to FORTAMET® compared to immediate-release metformin was also shown to be statistically smaller as seen by the 95% CI for the treatment difference which did not include zero.

Footnote: Patients were taking metformin-containing medications at baseline that were prescribed by their personal physicians.

The mean changes for FPG (Table 3) and plasma insulin (Table 3) were small for both FORTAMET® and immediate-release metformin, and were not clinically meaningful. Seventy-six (22%) and 49 (14%) of the FORTAMET® and immediate-release patients, respectively, discontinued prematurely from the trial. Eighteen (5%) patients on FORTAMET® withdrew because of a stated lack of efficacy, as compared with 8 patients (2%) on immediate-release metformin (p=0.047).

Results from this study also indicated that neither FORTAMET® nor immediate-release metformin were associated with weight gain or increases in body mass index.

A 24-week, double blind, placebo-controlled study of immediate-release metformin plus insulin, versus insulin plus placebo, was conducted in patients with type 2 diabetes who failed to achieve adequate glycemic control on insulin alone (Table 4). Patients randomized to receive immediate-release metformin plus insulin achieved a reduction in HbA1c of 2.10%, compared to a 1.56% reduction in HbA1c achieved by insulin plus placebo. The improvement in glycemic control was achieved at the final study visit with 16% less insulin, 93.0 U/day versus 110.6 U/day, immediate-release metformin plus insulin versus insulin plus placebo, respectively, p=0.04.

Table 4 Combined Immediate-Release Metformin/lnsulin vs. Placebo/Insulin: Summary of Mean Changes from Baseline in HbA1c and Daily Insulin Dose
 | Immediate-Release Metformin /Insulin (n = 26) | Placebo/Insulin (n = 28) | Treatment difference Mean ± SE
HbA1c (%)
Baseline | 8.95 | 9.32
Change at FINAL VISIT | -2.10 | -1.56 | -0.54 ± 0.43a
Insulin Dose (U/day)
Baseline | 93.12 | 94.64
Change at FINAL VISIT | -0.15 | 15.93 | -16.08 ± 7.77b

a Statistically significant using analysis of covariance with baseline as covariate (p=0.04). Not significant using analysis of variance (values shown in table)
b Statistically significant for insulin (p=0.04)

A second double-blind, placebo-controlled study (n=51), with 16 weeks of randomized treatment, demonstrated that in patients with type 2 diabetes controlled on insulin for 8 weeks with an average HbA1c of 7.46 ± 0.97%, the addition of immediate-release metformin maintained similar glycemic control (HbA1c 7.15 ± 0.61 versus 6.97 ± 0.62 for immediate-release metformin plus insulin and placebo plus insulin, respectively) with 19% less insulin versus baseline (reduction of 23.68 ± 30.22 versus an increase of 0.43 ± 25.20 units for immediate-release metformin plus insulin and placebo plus insulin, p less than 0.01). In addition, this study demonstrated that the combination of immediate-release metformin plus insulin resulted in reduction in body weight of 3.11 ± 4.30 lbs, compared to an increase of 1.30 ± 6.08 lbs for placebo plus insulin, p=0.01.

Pediatric Clinical Studies

No pediatric clinical studies have been conducted with FORTAMET®. In a double-blind, placebo-controlled study in pediatric patients aged 10 to 16 years with type 2 diabetes (mean FPG 182.2 mg/dL), treatment with immediate-release metformin (up to 2000 mg/day) for up to 16 weeks (mean duration of treatment 11 weeks) resulted in a significant mean net reduction in FPG of 64.3 mg/dL compared with placebo (Table 5).

Table 5 Immediate-Release Metformin vs. Placebo (Pediatricsa): Summary of Mean Changes from Baseline* in Plasma Glucose and Body Weight at Final Visit
 | Immediate-Release Metformin | Placebo | p-Value
FPG (mg/dL) | (n = 37) | (n = 36)
Baseline | 162.4 | 192.3
Change at FINAL VISIT | -42.9 | 21.4 | less than 0.001
Body Weight (lbs) | (n = 39) | (n = 38)
Baseline | 205.3 | 189.0
Change at FINAL VISIT | -3.3 | -2.0 | NS**

a Pediatric patients mean age 13.8 years (range 10-16 years)
* All patients on diet therapy at Baseline
** Not statistically significant

INDICATIONS AND USAGE

FORTAMET® is indicated as an adjunct to diet and exercise to improve glycemic control in adults with type 2 diabetes mellitus.

CONTRAINDICATIONS

FORTAMET® is contraindicated in patients with:

1. Renal disease or renal dysfunction (e.g., as suggested by serum creatinine levels ≥1.5 mg/dL [males], ≥1.4 mg/dL [females] or abnormal creatinine clearance) which may also result from conditions such as cardiovascular collapse (shock), acute myocardial infarction, and septicemia (see WARNINGS and PRECAUTIONS).
2. Known hypersensitivity to metformin.
3. Acute or chronic metabolic acidosis, including diabetic ketoacidosis, with or without coma. Diabetic ketoacidosis should be treated with insulin.

FORTAMET® should be temporarily discontinued in patients undergoing radiologic studies involving intravascular administration of iodinated contrast materials, because use of such products may result in acute alteration of renal function (see also PRECAUTIONS).

WARNINGS

Lactic Acidosis:

Lactic acidosis is a rare, but serious, metabolic complication that can occur due to metformin accumulation during treatment with FORTAMET® (metformin hydrochloride) Extended-Release Tablets; when it occurs, it is fatal in approximately 50% of cases. Lactic acidosis may also occur in association with a number of pathophysiologic conditions, including diabetes mellitus, and whenever there is significant tissue hypoperfusion and hypoxemia. Lactic acidosis is characterized by elevated blood lactate levels (>5 mmol/ L), decreased blood pH, electrolyte disturbances with an increased anion gap, and an increased lactate/pyruvate ratio. When metformin is implicated as the cause of lactic acidosis, metformin plasma levels >5 μg/mL are generally found.

The reported incidence of lactic acidosis in patients receiving metformin hydrochloride is very low (approximately 0.03 cases/1000 patient-years, with approximately 0.015 fatal cases/1000 patient-years). Reported cases have occurred primarily in diabetic patients with significant renal insufficiency, including both intrinsic renal disease and renal hypoperfusion, often in the setting of multiple concomitant medical/ surgical problems and multiple concomitant medications. Patients with congestive heart failure requiring pharmacologic management, in particular those with unstable or acute congestive heart failure who are at risk of hypoperfusion and hypoxemia, are at increased risk of lactic acidosis. The risk of lactic acidosis increases with the degree of renal dysfunction and the patient's age. The risk of lactic acidosis may, therefore, be significantly decreased by regular monitoring of renal function in patients taking FORTAMET® (metformin hydrochloride) Extended-Release Tablets and by use of the minimum effective dose of FORTAMET®. In particular, treatment of the elderly should be accompanied by careful monitoring of renal function. FORTAMET® treatment should not be initiated in patients ≥80 years of age unless measurement of creatinine clearance demonstrates that renal function is not reduced, as these patients are more susceptible to developing lactic acidosis. In addition, FORTAMET® should be promptly withheld in the presence of any condition associated with hypoxemia, dehydration, or sepsis. Because impaired hepatic function may significantly limit the ability to clear lactate, FORTAMET® should generally be avoided in patients with clinical or laboratory evidence of hepatic disease. Patients should be cautioned against excessive alcohol intake, either acute or chronic, when taking FORTAMET®, since alcohol potentiates the effects of metformin hydrochloride on lactate metabolism. In addition, FORTAMET® should be temporarily discontinued prior to any intravascular radiocontrast study and for any surgical procedure (see also PRECAUTIONS).

The onset of lactic acidosis often is subtle, and accompanied only by nonspecific symptoms such as malaise, myalgias, respiratory distress, increasing somnolence, and nonspecific abdominal distress. There may be associated hypothermia, hypotension, and resistant bradyarrhythmias with more marked acidosis. The patient and the patient's physician must be aware of the possible importance of such symptoms and the patient should be instructed to notify the physician immediately if they occur (see also PRECAUTIONS). FORTAMET® should be withdrawn until the situation is clarified. Serum electrolytes, ketones, blood glucose and, if indicated, blood pH, lactate levels, and even blood metformin levels may be useful. Once a patient is stabilized on any dose level of FORTAMET®, gastrointestinal symptoms, which are common during initiation of therapy, are unlikely to be drug related. Later occurrence of gastrointestinal symptoms could be due to lactic acidosis or other serious disease.

Levels of fasting venous plasma lactate above the upper limit of normal but less than 5 mmol/L in patients taking FORTAMET® do not necessarily indicate impending lactic acidosis and may be explainable by other mechanisms, such as poorly controlled diabetes or obesity, vigorous physical activity, or technical problems in sample handling (see also PRECAUTIONS).

Lactic acidosis should be suspected in any diabetic patient with metabolic acidosis lacking evidence of ketoacidosis (ketonuria and ketonemia).

Lactic acidosis is a medical emergency that must be treated in a hospital setting. In a patient with lactic acidosis who is taking FORTAMET®, the drug should be discontinued immediately and general supportive measures promptly instituted. Because metformin hydrochloride is dialyzable (with a clearance of up to 170 mL/min under good hemodynamic conditions), prompt hemodialysis is recommended to correct the acidosis and remove the accumulated metformin. Such management often results in prompt reversal of symptoms and recovery (see also CONTRAINDICATIONS and PRECAUTIONS).

PRECAUTIONS

Enter section text here

General

Monitoring of renal function - Metformin is known to be substantially excreted by the kidney, and the risk of metformin accumulation and lactic acidosis increases with the degree of impairment of renal function. Thus, patients with serum creatinine levels above the upper limit of normal for their age should not receive FORTAMET®. In patisents with advanced age, FORTAMET® should be carefully titrated to establish the minimum dose for adequate glycemic effect, because aging is associated with reduced renal function. In elderly patients, particularly those ≥80 years of age, renal function should be monitored regularly and, generally, FORTAMET® should not be titrated to the maximum dose (see WARNINGS and DOSAGE AND ADMINISTRATION).

Before initiation of FORTAMET® therapy and at least annually thereafter, renal function should be assessed and verified as normal. In patients in whom development of renal dysfunction is anticipated, renal function should be assessed more frequently and FORTAMET® discontinued if evidence of renal impairment is present.

Macrovascular Outcomes -

There have been no clinical studies establishing conclusive evidence of macrovascular risk reduction with FORTAMET® or any other anti-diabetic drug.

Use of concomitant medications that may affect renal function or metformin disposition - Concomitant medication(s) that may affect renal function or result in significant hemodynamic change or may interfere with the disposition of metformin, such as cationic drugs that are eliminated by renal tubular secretion (see PRECAUTIONS: Drug Interactions), should be used with caution.

Radiologic studies involving the use of intravascular iodinated contrast materials (for example, intravenous urogram, intravenous cholangiography, angiography, and computed tomography (CT) scans with intravascular contrast materials) – Intravascular contrast studies with iodinated materials can lead to acute alteration of renal function and have been associated with lactic acidosis in patients receiving metformin (see CONTRAINDICATIONS). Therefore, in patients in whom any such study is planned, FORTAMET® should be temporarily discontinued at the time of or prior to the procedure, and withheld for 48 hours subsequent to the procedure and reinstituted only after renal function has been re-evaluated and found to be normal.

Hypoxic states – Cardiovascular collapse (shock) from whatever cause, acute congestive heart failure, acute myocardial infarction and other conditions characterized by hypoxemia have been associated with lactic acidosis and may also cause prerenal azotemia. When such events occur in patients on FORTAMET® therapy, the drug should be promptly discontinued.

Surgical procedures – FORTAMET® therapy should be temporarily suspended for any surgical procedure (except minor procedures not associated with restricted intake of food and fluids) and should not be restarted until the patient's oral intake has resumed and renal function has been evaluated as normal.

Alcohol intake – Alcohol is known to potentiate the effect of metformin on lactate metabolism. Patients, therefore, should be warned against excessive alcohol intake, acute or chronic, while receiving FORTAMET®.

Impaired hepatic function – Since impaired hepatic function has been associated with some cases of lactic acidosis, FORTAMET® should generally be avoided in patients with clinical or laboratory evidence of hepatic disease.

Vitamin B12 levels – In controlled clinical trials of immediate-release metformin of 29 weeks duration, a decrease to subnormal levels of previously normal serum Vitamin B12 levels, without clinical manifestations, was observed in approximately 7% of patients. Such decrease, possibly due to interference with B12 absorption from the B12 -intrinsic factor complex, is, however, very rarely associated with anemia and appears to be rapidly reversible with discontinuation of immediate-release metformin or Vitamin B12 supplementation. Measurement of hematologic parameters on an annual basis is advised in patients on FORTAMET® and any apparent abnormalities should be appropriately investigated and managed (see PRECAUTIONS: Laboratory Tests). Certain individuals (those with inadequate Vitamin B12 or calcium intake or absorption) appear to be predisposed to developing subnormal Vitamin B12 levels. In these patients, routine serum Vitamin B12 measurements at two- to three-year intervals may be useful.

Change in clinical status of patients with previously controlled type 2 diabetes – A patient with type 2 diabetes previously well controlled on FORTAMET® who develops laboratory abnormalities or clinical illness (especially vague and poorly defined illness) should be evaluated promptly for evidence of ketoacidosis or lactic acidosis. Evaluation should include serum electrolytes and ketones, blood glucose and, if indicated, blood pH, lactate, pyruvate, and metformin levels. If acidosis of either form occurs, FORTAMET® must be stopped immediately and other appropriate corrective measures initiated (see also WARNINGS).

Hypoglycemia – Hypoglycemia does not occur in patients receiving FORTAMET® alone under usual circumstances of use, but could occur when caloric intake is deficient, when strenuous exercise is not compensated by caloric supplementation, or during concomitant use with other glucose-lowering agents (such as sulfonylureas and insulin) or ethanol. Elderly, debilitated, or malnourished patients, and those with adrenal or pituitary insufficiency or alcohol intoxication are particularly susceptible to hypoglycemic effects. Hypoglycemia may be difficult to recognize in the elderly, and in people who are taking beta-adrenergic blocking drugs.

Loss of control of blood glucose – When a patient stabilized on any diabetic regimen is exposed to stress such as fever, trauma, infection, or surgery, a temporary loss of glycemic control may occur. At such times, it may be necessary to withhold FORTAMET® and temporarily administer insulin. FORTAMET® may be reinstituted after the acute episode is resolved.

The effectiveness of oral antidiabetic drugs in lowering blood glucose to a targeted level decreases in many patients over a period of time. This phenomenon, which may be due to progression of the underlying disease or to diminished responsiveness to the drug, is known as secondary failure, to distinguish it from primary failure in which the drug is ineffective during initial therapy. Should secondary failure occur with FORTAMET® or sulfonylurea monotherapy, combined therapy with FORTAMET® and sulfonylurea may result in a response. Should secondary failure occur with combined FORTAMET®/sulfonylurea therapy, it may be necessary to consider therapeutic alternatives including initiation of insulin therapy.

Information for Patients

Patients should be informed of the potential risks and benefits of FORTAMET® and of alternative modes of therapy. They should also be informed about the importance of adherence to dietary instructions, of a regular exercise program, and of regular testing of blood glucose, glycosylated hemoglobin, renal function, and hematologic parameters.

The risks of lactic acidosis, its symptoms, and conditions that predispose to its development, as noted in the WARNINGS and PRECAUTIONS sections, should be explained to patients. Patients should be advised to discontinue FORTAMET® immediately and to promptly notify their health practitioner if unexplained hyperventilation, myalgia, malaise, unusual somnolence, or other nonspecific symptoms occur. Once a patient is stabilized on any dose level of FORTAMET®, gastrointestinal symptoms, which are common during initiation of metformin therapy, are unlikely to be drug related. Later occurrence of gastrointestinal symptoms could be due to lactic acidosis or other serious disease.

Patients should be counseled against excessive alcohol intake, either acute or chronic, while receiving FORTAMET®.

FORTAMET® alone does not usually cause hypoglycemia, although it may occur when FORTAMET® is used in conjunction with oral sulfonylureas and insulin. When initiating combination therapy, the risks of hypoglycemia, its symptoms and treatment, and conditions that predispose to its development should be explained to patients and responsible family members (see Patient Information Printed Below).

Patients should be informed that FORTAMET® must be swallowed whole and not chewed, cut, or crushed, and that the inactive ingredients may occasionally be eliminated in the feces as a soft mass that may resemble the original tablet (see Patient Information).

Laboratory Tests

Response to all diabetic therapies should be monitored by periodic measurements of fasting blood glucose and glycosylated hemoglobin levels, with a goal of decreasing these levels toward the normal range. During initial dose titration, fasting glucose can be used to determine the therapeutic response. Thereafter, both glucose and glycosylated hemoglobin should be monitored. Measurements of glycosylated hemoglobin may be especially useful for evaluating long-term control (see also DOSAGE AND ADMINISTRATION).

Initial and periodic monitoring of hematologic parameters (e.g., hemoglobin/hematocrit and red blood cell indices) and renal function (serum creatinine) should be performed, at least on an annual basis. While megaloblastic anemia has rarely been seen with immediate-release metformin therapy, if this is suspected, Vitamin B12 deficiency should be excluded.

Drug Interactions (Clinical Evaluation of Drug Interactions Conducted with Immediate-Release Metformin)

Glyburide– In a single-dose interaction study in type 2 diabetes patients, co-administration of metformin and glyburide did not result in any changes in either metformin pharmacokinetics or pharmacodynamics. Decreases in glyburide AUC and Cmax were observed, but were highly variable. The single-dose nature of this study and the lack of correlation between glyburide blood levels and pharmacodynamic effects, makes the clinical significance of this interaction uncertain (see DOSAGE AND ADMINISTRATION: Concomitant FORTAMET® and Oral Sulfonylurea Therapy in Adult Patients).

Furosemide– A single-dose, metformin-furosemide drug interaction study in healthy subjects demonstrated that pharmacokinetic parameters of both compounds were affected by co-administration. Furosemide increased the metformin plasma and blood Cmax by 22% and blood AUC by 15%, without any significant change in metformin renal clearance. When administered with metformin, the Cmax and AUC of furosemide were 31% and 12% smaller, respectively, than when administered alone, and the terminal half-life was decreased by 32%, without any significant change in furosemide renal clearance. No information is available about the interaction of metformin and furosemide when co-administered chronically.

Nifedipine– A single-dose, metformin-nifedipine drug interaction study in normal healthy volunteers demonstrated that co-administration of nifedipine increased plasma metformin Cmax and AUC by 20% and 9%, respectively, and increased the amount excreted in the urine. Tmax and half-life were unaffected. Nifedipine appears to enhance the absorption of metformin. Metformin had minimal effects on nifedipine.

Cationic drugs– Cationic drugs (e.g., amiloride, digoxin, morphine, procainamide, quinidine, quinine, ranitidine, triamterene, trimethoprim, or vancomycin) that are eliminated by renal tubular secretion theoretically have the potential for interaction with metformin by competing for common renal tubular transport systems. Such interaction between metformin and oral cimetidine has been observed in normal healthy volunteers in both single- and multiple-dose, metformin-cimetidine drug interaction studies, with a 60% increase in peak metformin plasma and whole blood concentrations and a 40% increase in plasma and whole blood metformin AUC. There was no change in elimination half-life in the single-dose study. Metformin had no effect on cimetidine pharmacokinetics. Although such interactions remain theoretical (except for cimetidine), careful patient monitoring and dose adjustment of FORTAMET® and/or the interfering drug is recommended in patients who are taking cationic medications that are excreted via the proximal renal tubular secretory system.

Other– Certain drugs tend to produce hyperglycemia and may lead to loss of glycemic control. These drugs include the thiazides and other diuretics, corticosteroids, phenothiazines, thyroid products, estrogens, oral contraceptives, phenytoin, nicotinic acid, sympathomimetics, calcium channel blocking drugs, and isoniazid. When such drugs are administered to a patient receiving FORTAMET®, the patient should be closely observed for loss of blood glucose control. When such drugs are withdrawn from a patient receiving FORTAMET®, the patient should be observed closely for hypoglycemia.

In healthy volunteers, the pharmacokinetics of metformin and propranolol, and metformin and ibuprofen were not affected when co-administered in single-dose interaction studies.

Metformin is negligibly bound to plasma proteins and is, therefore, less likely to interact with highly protein-bound drugs such as salicylates, sulfonamides, chloramphenicol, and probenecid, as compared to the sulfonylureas, which are extensively bound to serum proteins.

Carcinogenesis, Mutagenesis, Impairment of Fertility

Long-term carcinogenicity studies with metformin have been performed in rats (dosing duration of 104 weeks) and mice (dosing duration of 91 weeks) at doses up to and including 900 mg/kg/day and 1500 mg/kg/day, respectively. These doses are both approximately four times the maximum recommended human daily dose of 2000 mg based on body surface area comparisons. No evidence of carcinogenicity with metformin was found in either male or female mice. Similarly, there was no tumorigenic potential observed with metformin in male rats. There was, however, an increased incidence of benign stromal uterine polyps in female rats treated with 900 mg/kg/day.

There was no evidence of mutagenic potential of metformin in the following in vitro tests: Ames test (S. typhimurium), gene mutation test (mouse lymphoma cells), or chromosomal aberrations test (human lymphocytes). Results in the in vivo mouse micronucleus test were also negative.

Fertility of male or female rats was unaffected by metformin when administered at doses as high as 600 mg/kg/day, which is approximately three times the maximum recommended human daily dose based on body surface area comparisons.

Pregnancy

Teratogenic Effects: Pregnancy Category B

Recent information strongly suggests that abnormal blood glucose levels during pregnancy are associated with a higher incidence of congenital abnormalities. Most experts recommend that insulin be used during pregnancy to maintain blood glucose levels as close to normal as possible. Because animal reproduction studies are not always predictive of human response, FORTAMET® should not be used during pregnancy unless clearly needed.

There are no adequate and well-controlled studies in pregnant women with immediate-release metformin or FORTAMET®. Metformin was not teratogenic in rats and rabbits at doses up to 600 mg/kg/day. This represents an exposure of about two and six times the maximum recommended human daily dose of 2000 mg based on body surface area comparisons for rats and rabbits, respectively. Determination of fetal concentrations demonstrated a partial placental barrier to metformin.

Nursing Mothers

Studies in lactating rats show that metformin is excreted into milk and reaches levels comparable to those in plasma. Similar studies have not been conducted in nursing mothers. Because the potential for hypoglycemia in nursing infants may exist, a decision should be made whether to discontinue nursing or to discontinue the drug, taking into account the importance of the drug to the mother. If FORTAMET® is discontinued, and if diet alone is inadequate for controlling blood glucose, insulin therapy should be considered.

Pediatric Use

No pediatric clinical studies have been conducted with FORTAMET®. The safety and effectiveness of immediate-release metformin for the treatment of type 2 diabetes have been established in pediatric patients ages 10 to 16 years (studies have not been conducted in pediatric patients below the age of 10 years). Use of immediate-release metformin in this age group is supported by evidence from adequate and well-controlled studies of immediate-release metformin in adults with additional data from a controlled clinical study in pediatric patients ages 10-16 years with type 2 diabetes, which demonstrated a similar response in glycemic control to that seen in adults (see CLINICAL PHARMACOLOGY: Pediatric Clinical Studies). In this study, adverse effects were similar to those described in adults (see ADVERSE REACTIONS: Pediatric Patients). A maximum daily dose of 2000 mg of immediate-release metformin is recommended.

The safety and efficacy of FORTAMET® has not been evaluated in pediatric patients.

Geriatric Use

Of the 389 patients who received FORTAMET® in controlled Phase III clinical studies, 26.5% [103/389] were 65 years and older. No overall differences in effectiveness or safety were observed between these patients and younger patients.

Controlled clinical studies of immediate-release metformin did not include sufficient numbers of elderly patients to determine whether they respond differently from younger patients, although other reported clinical experience has not identified differences in responses between the elderly and younger patients. Metformin is known to be substantially excreted by the kidney and because of the risk of serious adverse reactions to the drug is greater in patients with impaired renal function, immediate-release metformin should only be used in patients with normal renal function (see CONTRAINDICATIONS, WARNINGS, and CLINICAL PHARMACOLOGY: Pharmacokinetics). Because aging is associated with reduced renal function, immediate-release metformin should be used with caution as age increases. Care should be taken in dose selection and should be based on careful and regular monitoring of renal function. Generally, elderly patients should not be titrated to the maximum dose of immediate-release metformin (see also WARNINGS and DOSAGE AND ADMINISTRATION).

ADVERSE REACTIONS

Enter section text here

FORTAMET® Clinical Studies

In the controlled clinical studies of FORTAMET® in patients with type 2 diabetes, a total of 424 patients received FORTAMET® therapy (up to 2500 mg/day) and 430 patients received immediate-release metformin. Adverse reactions reported in ≥5% of the FORTAMET® or immediate-release metformin patients are listed in Table 6. These pooled results show that the most frequently reported adverse reactions in the FORTAMET® group were infection, diarrhea, and nausea. Similar incidences of these adverse reactions were seen in the immediate-release metformin group.

Table 6 Number and Percentage of Patients With the Most Common (Incidence ≥5%)Treatment-Emergent Signs or Symptoms by Body System and Preferred Term - Pooled Phase II and III Studies
 | FORTAMET® (N=424) | Immediate-Release Metformin (N=430)
Body System Preferred Term | n | (%) | n | (%)
Body as a Whole
Accidental Injury | 31 | (7.3) | 24 | (5.6)
Headache | 20 | (4.7) | 22 | (5.1)
Infection | 87 | (20.5) | 90 | (20.9)
Digestive System
Diarrhea | 71 | (16.7) | 51 | (11.9)
Dyspepsia | 18 | (4.2) | 22 | (5.1)
Nausea | 36 | (8.5) | 32 | (7.4)
Respiratory System
Rhinitis | 18 | (4.2) | 24 | (5.6)

The most frequent adverse events thought to be related to FORTAMET® were diarrhea, nausea, dyspepsia, flatulence, and abdominal pain. The frequency of dyspepsia was 4.2% in the FORTAMET® group compared to 5.1% in the immediate-release group, the frequency of flatulence was 3.5% in the FORTAMET® group compared to 3.7% in the immediate-release group, and the frequency of abdominal pain was 3.3% in the FORTAMET® group compared to 4.4% in the immediate-release group.

In the controlled studies, 4.7% of patients treated with FORTAMET® and 4.9% of patients treated with immediate-release metformin were discontinued due to adverse events.

Immediate-Release Metformin Phase III Clinical Studies

In a U.S. double-blind clinical study of immediate-release metformin in patients with type 2 diabetes, a total of 141 patients received immediate-release metformin therapy (up to 2550 mg per day) and 145 patients received placebo. Adverse reactions reported in greater than 5% of the immediate-release metformin patients, and that were more common in immediate-release metformin than placebo-treated patients, are listed in Table 7.

Table 7 Most Common Adverse Reactions (>5.0%) in a Placebo-Controlled Clinical Study of Immediate-Release Metformin Monotherapy*
 | Immediate-Release Metformin Monotherapy (n = 141) | Placebo (n = 145)
Adverse Reaction | % of Patients
Diarrhea | 53.2 | 11.7
Nausea/Vomiting | 25.5 | 8.3
Flatulence | 12.1 | 5.5
Asthenia | 9.2 | 5.5
Indigestion | 7.1 | 4.1
Abdominal Discomfort | 6.4 | 4.8
Headache | 5.7 | 4.8

* Reactions that were more common in immediate-release metformin that placebo-treated patients

Diarrhea led to discontinuation of study medication in 6% of patients treated with immediate-release metformin. Additionally, the following adverse reactions were reported in ≥1.0 - ≤5.0% of immediate-release metformin patients and were more commonly reported with immediate-release metformin than placebo: abnormal stools, hypoglycemia, myalgia, lightheaded, dyspnea, nail disorder, rash, sweating increased, taste disorder, chest discomfort, chills, flu syndrome, flushing, palpitation.

Pediatric Patients

No pediatric clinical studies have been conducted with FORTAMET®. In clinical trials with immediate-release metformin in pediatric patients with type 2 diabetes, the profile of adverse reactions was similar to that observed in adults.

OVERDOSAGE

Hypoglycemia has not been seen even with ingestion of up to 85 grams of immediate-release metformin, although lactic acidosis has occurred in such circumstances (see WARNINGS). Metformin is dialyzable with a clearance of up to 170 mL/min under good hemodynamic conditions. Therefore, hemodialysis may be useful for removal of accumulated drug from patients in whom metformin over-dosage is suspected.

DOSAGE AND ADMINISTRATION

There is no fixed dosage regimen for the management of hyperglycemia in patients with type 2 diabetes with FORTAMET® or any other pharmacologic agent. Dosage of FORTAMET® must be individualized on the basis of both effectiveness and tolerance, while not exceeding the maximum recommended daily dose. The maximum recommended daily dose of FORTAMET® Extended-Release Tablets in adults is 2500 mg.

FORTAMET® should be taken with a full glass of water once daily with the evening meal. FORTAMET® should be started at a low dose, with gradual dose escalation, both to reduce gastrointestinal side effects and to permit identification of the minimum dose required for adequate glycemic control of the patient.

During treatment initiation and dose titration (see Recommended Dosing Schedule), fasting plasma glucose should be used to determine the therapeutic response to FORTAMET® and identify the minimum effective dose for the patient. Thereafter, glycosylated hemoglobin should be measured at intervals of approximately three months. The therapeutic goal should be to decrease both fasting plasma glucose and glycosylated hemoglobin levels to normal or near normal by using the lowest effective dose of FORTAMET®, either when used as monotherapy or in combination with sulfonylurea or insulin.

Monitoring of blood glucose and glycosylated hemoglobin will also permit detection of primary failure, i.e., inadequate lowering of blood glucose at the maximum recommended dose of medication, and secondary failure, i.e., loss of an adequate blood glucose lowering response after an initial period of effectiveness.

Short-term administration of FORTAMET® may be sufficient during periods of transient loss of control in patients usually well-controlled on diet alone.

Recommended Dosing Schedule

The usual starting dose of FORTAMET® (metformin hydrochloride) Extended-Release Tablets is 1000 mg taken with a full glass of water once daily with the evening meal, although 500 mg may be utilized when clinically appropriate. Dosage increases should be made in increments of 500 mg weekly, up to a maximum of 2500 mg once daily with the evening meal (see CLINICAL PHARMACOLOGY, Clinical Studies).

In randomized trials, patients currently treated with immediate-release metformin were switched to FORTAMET®. Results of this trial suggest that patients receiving immediate-release metformin treatment may be safely switched to FORTAMET® once daily at the same total daily dose, up to 2500 mg once daily. Following a switch from immediate-release metformin to FORTAMET®, glycemic control should be closely monitored and dosage adjustments made accordingly (see CLINICAL PHARMACOLOGY, Clinical Studies).

Pediatrics – There is no pediatric information available for FORTAMET®.

Transfer From Other Antidiabetic Therapy

When transferring patients from standard oral hypoglycemic agents other than chlorpropamide to FORTAMET®, no transition period generally is necessary. When transferring patients from chlorpropamide, care should be exercised during the first two weeks because of the prolonged retention of chlorpropamide in the body, leading to overlapping drug effects and possible hypoglycemia.

Concomitant FORTAMET® and Oral Sulfonylurea Therapy in Adult Patients

If patients have not responded to four weeks of the maximum dose of FORTAMET® monotherapy, consideration should be given to gradual addition of an oral sulfonylurea while continuing FORTAMET® at the maximum dose, even if prior primary or secondary failure to a sulfonylurea has occurred. Clinical and pharmacokinetic drug-drug interaction data are currently available only for metformin plus glyburide (also known as glibenclamide). With concomitant FORTAMET® and sulfonylurea therapy, the desired control of blood glucose may be obtained by adjusting the dose of each drug. However, attempts should be made to identify the minimum effective dose of each drug to achieve this goal. With concomitant FORTAMET® and sulfonylurea therapy, the risk of hypoglycemia associated with sulfonylurea therapy continues and may be increased. Appropriate precautions should be taken (see Package Insert of the respective sulfonylurea).

If patients have not satisfactorily responded to one to three months of concomitant therapy with the maximum dose of FORTAMET® and the maximum dose of an oral sulfonylurea, consider therapeutic alternatives including switching to insulin with or without FORTAMET®.

Concomitant FORTAMET® and Insulin Therapy in Adult Patients

The current insulin dose should be continued upon initiation of FORTAMET® therapy. FORTAMET® therapy should be initiated at 500 mg once daily in patients on insulin therapy. For patients not responding adequately, the dose of FORTAMET® should be increased by 500 mg after approximately 1 week and by 500 mg every week thereafter until adequate glycemic control is achieved. The maximum recommended daily dose for FORTAMET® Extended-Release Tablets is 2500 mg. It is recommended that the insulin dose be decreased by 10% to 25% when fasting plasma glucose concentrations decrease to less than 120 mg/dL in patients receiving concomitant insulin and FORTAMET®. Further adjustment should be individualized based on glucose-lowering response.

Specific Patient Populations

FORTAMET® is not recommended for use in pregnancy, and is not recommended in patients below the age of 17 years.

The initial and maintenance dosing of FORTAMET® should be conservative in patients with advanced age, due to the potential for decreased renal function in this population. Any dosage adjustment should be based on a careful assessment of renal function. Generally, elderly, debilitated, and malnourished patients should not be titrated to the maximum dose of FORTAMET®.

Monitoring of renal function is necessary to aid in prevention of lactic acidosis, particularly in the elderly (see WARNINGS).

HOW SUPPLIED

FORTAMET® (metformin hydrochloride) Extended-Release Tablets are supplied as biconvex-shaped, film-coated extended-release tablets containing 500 mg or 1000 mg of metformin hydrochloride.

500 mg extended-release, white-colored tablets imprinted with Andrx logo and 574 on one side: bottles of 60 (NDC 54868-5558-0); and in bottles of 90 (NDC 54868-5558-1).

1000 mg extended-release, white-colored tablets imprinted with Andrx logo and 575 on one side: bottles of 30 (NDC 54868-2894-0).

STORAGE

Store at 20-25°C (68-77°F) - Excursions permitted to 15° - 30°C (59° - 86°F) [See USP Controlled Room Temperature]. Keep tightly closed (protect from moisture). Protect from light. Avoid excessive heat and humidity.

Distributed by:
Sciele Pharma, Inc.
Atlanta, GA 30328

Manufactured by:
Watson Laboratories - Florida
Ft. Lauderdale, FL 33314

Relabeling and Repackaging by:
Physicians Total Care, Inc.
Tulsa, OK 74146

PATIENT INFORMATION ABOUT FORTAMET® (metformin hydrochloride) Extended-Release Tablets

Q1. Why do I need to take FORTAMET®?

Your doctor has prescribed FORTAMET® to treat your type 2 diabetes, a condition in which blood sugar (blood glucose) is elevated. There are two types of diabetes. FORTAMET® is indicated for the most common type, known as type 2 diabetes.

Q2. Why is it important to control type 2 diabetes?

Type 2 diabetes has multiple possible complications, including blindness, kidney failure, and circulatory and heart problems. Lowering your blood sugar to a normal level may prevent or delay these complications.

Q3. How is type 2 diabetes usually controlled?

High blood sugar can be lowered by diet and exercise, by a number of oral medications and by insulin injections. Your doctor may recommend that you try lifestyle modifications such as improved diet and exercise before initiating drug treatment for type 2 diabetes. Each patient will be treated individually by his or her physician, and should follow all treatment recommendations.

Q4. Does FORTAMET® work differently from other glucose control medications?

Yes. FORTAMET®, as well as other formulations of metformin, lowers the amount of sugar in your blood by controlling how much sugar is released by the liver. FORTAMET® (metformin hydrochloride) does not cause your body to produce more insulin. FORTAMET® rarely causes hypoglycemia (low blood sugar) and it does not usually cause weight gain when taken alone. However, if you do not eat enough, if you take other medications to lower blood sugar, or if you drink alcohol, you can develop hypoglycemia. Specifically, when FORTAMET® is taken together with a sulfonylurea or with insulin, hypoglycemia and weight gain are more likely to occur.

Q5. What happens if my blood sugar is still too high?

If your blood sugar is high, consult your physician. When blood sugar cannot be lowered enough by either FORTAMET® (metformin hydrochloride) Extended-Release Tablets or a sulfonylurea, the two medications can be effective when taken together. Other alternatives involve switching to other oral antidiabetic drugs (e.g., alpha glucoside inhibitors or glitazones). FORTAMET® may be stopped and replaced with other drugs and/or insulin. If you are unable to maintain your blood sugar with diet, exercise and glucose-control medications taken orally, then your doctor may prescribe injectable insulin to control your diabetes.

Q6. Why should I take FORTAMET® in addition to insulin if I am already on insulin alone?

Adding FORTAMET® to insulin can help you better control your blood sugar while reducing the insulin dose and possibly reducing your weight.

Q7. Can FORTAMET® cause side effects?

FORTAMET®, like all blood sugar-lowering medications, can cause side effects in some patients. Most of these side effects are minor and will go away after you've taken FORTAMET® for a while. However, there are also serious but rare side effects related to FORTAMET® (see below).

Q8. What kind of side effects can FORTAMET® cause?

If side effects occur, they usually occur during the first few weeks of therapy. They are normally minor ones such as diarrhea, nausea, abdominal pain and upset stomach. FORTAMET® is generally taken with meals, which reduce these side effects.

Although these side effects are likely to go away, call your doctor if you have severe discomfort or if these effects last for more than a few weeks. Some patients may need to have their doses lowered or stop taking FORTAMET®, either temporarily or permanently. You should tell your doctor if the problems come back or start later on during the therapy.

WARNING: A rare number of people who have taken metformin have developed a serious condition called lactic acidosis. Properly functioning kidneys are needed to help prevent lactic acidosis. You should not take FORTAMET® if you have impaired kidney function, as measured by a blood test (see Q9-13).

Q9. Are there any serious side effects that FORTAMET® can cause?

FORTAMET® rarely causes serious side effects. The most serious side effect that FORTAMET® can cause is called lactic acidosis.

Q10. What is lactic acidosis and can it happen to me?

Lactic acidosis is caused by a build-up of lactic acid in the blood. Lactic acidosis associated with metformin is rare and has occurred mostly in people whose kidneys were not working normally. Lactic acidosis has been reported in about one in 33,000 patients taking metformin over the course of a year. Although rare, if lactic acidosis does occur, it can be fatal in up to half the cases.

It is also important for your liver to be working normally when you take FORTAMET®. Your liver helps to remove lactic acid from your bloodstream. Your doctor will monitor your diabetes and may perform blood tests on you from time to time to make sure your kidneys and your liver are functioning normally. There is no evidence that FORTAMET® causes harm to the kidneys or liver.

Q11. Are there other risk factors for lactic acidosis?

Your risk of developing lactic acidosis from taking FORTAMET® is very low as long as your kidneys and liver are healthy. However, some factors can increase your risk because they can affect kidney and liver function. You should discuss your risk with your physician. You should not take FORTAMET® if:

- You have some forms of kidney or liver problems
- You have congestive heart failure which is treated with medications, e.g., digoxin (Lanoxin®) or furosemide (Lasix®)
- You drink alcohol excessively (all the time or short-term “binge” drinking)
- You are seriously dehydrated (have lost a large amount of body fluids)
- You are going to have, within a few days, certain x-ray tests with injectable contrast agents
- You are going to have surgery
- You develop a serious condition such as a heart attack, severe infection, or a stroke
- You are 80 years of age or older and have NOT had your kidney function tested

Q12. What are the symptoms of lactic acidosis?

Some of the symptoms include feeling very weak, tired or uncomfortable, unusual muscle pain, trouble breathing, unusual or unexpected stomach discomfort, feeling cold, feeling dizzy or lightheaded, or suddenly developing a slow or irregular heartbeat. If you notice these symptoms, or if your medical condition has suddenly changed, stop taking FORTAMET® and call your doctor right away. Lactic acidosis is a medical emergency that must be treated in a hospital.

Q13. What does my doctor need to know to decrease my risk of lactic acidosis?

Tell your doctor if you have an illness that results in severe vomiting, diarrhea and/or fever, or if your intake of fluids is generally reduced. These situations can lead to severe dehydration, and it may be necessary to stop taking FORTAMET® temporarily. You should let your doctor know if you are going to have any surgery or specialized x-ray procedures that require injection of contrast agents. FORTAMET® therapy will need to be stopped temporarily in such instances.

Q14. Can I take FORTAMET® with other medications?

Remind your doctor and/or pharmacist that you are taking FORTAMET® when any new drug is prescribed or a change is made in how you take a drug already prescribed. FORTAMET® may interfere with the way some drugs work and some drugs may interfere with the action of FORTAMET®.

Q15. What if I become pregnant while taking FORTAMET®?

Tell your doctor if you plan to become pregnant or have become pregnant. As with other oral glucose-control medications, you should not take FORTAMET® during pregnancy. Usually your doctor will prescribe insulin while you are pregnant.

Q16. How do I take FORTAMET®?

FORTAMET® tablets should not be cut, crushed, or chewed and should be taken whole with a full glass of water once daily with the evening meal. Occasionally, the inactive ingredients of FORTAMET® may be eliminated as a soft mass in your stool that may look like the original tablet; this is not harmful and will not effect the way FORTAMET® works to control diabetes. FORTAMET® should be taken once a day with food. You will be started on a low dose of FORTAMET® and your dosage will be increased gradually until your blood sugar is controlled.

Q17. Where can I get more information about FORTAMET®?

This leaflet is a summary of the most important information about FORTAMET®. If you have any questions or problems, you should talk to your doctor or other healthcare provider about type 2 diabetes as well as FORTAMET® and its side effects.

Distributed by:
Sciele Pharma, Inc.
Atlanta, GA 30328

Manufactured by:
Watson Laboratories - Florida
Ft. Lauderdale, FL 33314

www.Fortamet.com

FORT-PI-08 Rev. 07/08 74200708

U.S. patent numbers 6,495,162; 6,866,866; 6,790,459; 6,099,859 - additional patents pending.

PRINCIPAL DISPLAY PANEL

FORTAMET® (metformin hydrochloride) Extended-Release Tablets

500 mg

1000 mg